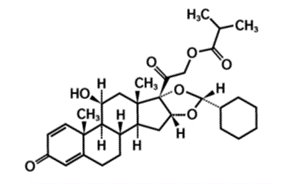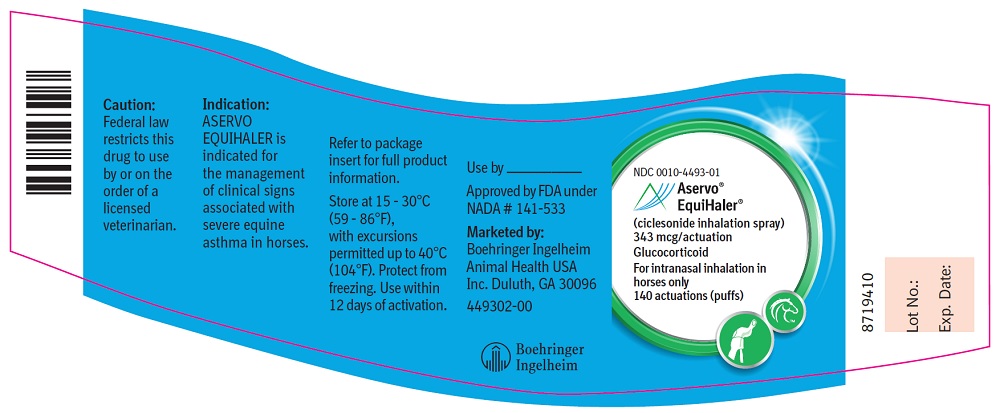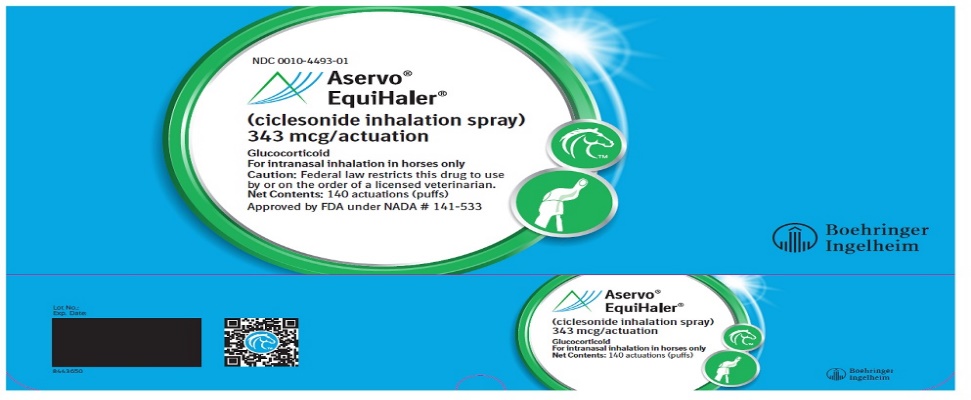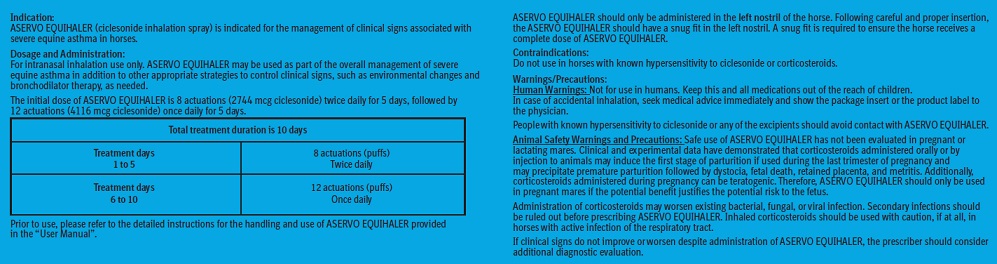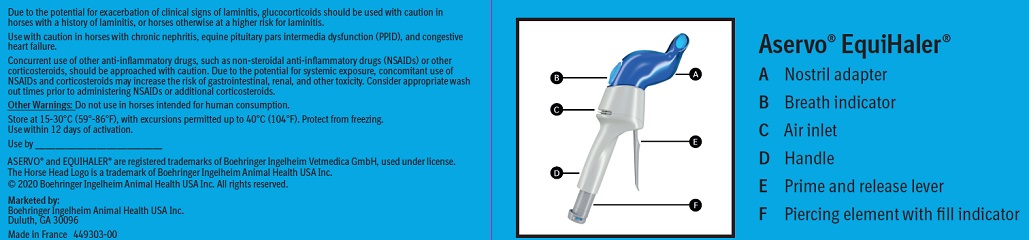 DRUG LABEL: Aservo EquiHaler
NDC: 0010-4493 | Form: SPRAY, METERED
Manufacturer: Boehringer Ingelheim Animal Health USA Inc.
Category: animal | Type: PRESCRIPTION ANIMAL DRUG LABEL
Date: 20210916

ACTIVE INGREDIENTS: CICLESONIDE 343 ug/1 1

Aservo® EquiHaler®
(ciclesonide inhalation spray)
343 mcg/actuation
Glucocorticoid
For intranasal inhalation in horses only

Caution:

Federal law restricts this drug to use by or on the order of a licensed veterinarian.

Description:

ASERVO EQUIHALER (ciclesonide inhalation spray) is a non-pressurized metered dose inhaler and drug cartridge combination containing a solution of 30 mg/mL of the prodrug ciclesonide, which is enzymatically converted to the pharmacologically active metabolite desisobutyrylciclesonide (des-ciclesonide) following inhalation. Des-ciclesonide is a glucocorticoid class of corticosteroid. Each actuation releases 343 mcg of ciclesonide. Inactive carrier ingredients include alcohol, purified water, and hydrochloric acid. The structural formula for ciclesonide is:

Indication:

ASERVO EQUIHALER is indicated for the management of clinical signs associated with severe equine asthma in horses.

Dosage and Administration:

For intranasal inhalation use only. ASERVO EQUIHALER may be used as part of the overall management of severe equine asthma in addition to other appropriate strategies to control clinical signs, such as environmental changes and bronchodilator therapy, as needed.

The initial dose of ASERVO EQUIHALER is 8 actuations (2744 mcg ciclesonide) twice daily for 5 days, followed by 12 actuations (4116 mcg ciclesonide) once daily for 5 days.

Total treatment duration is 10 days
Treatment days; 1 to 5 | 8 actuations (puffs); Twice daily
Treatment days; 6 to 10 | 12 actuations (puffs); Once daily

Prior to use, please refer to the detailed instructions for the handling and use of ASERVO EQUIHALER provided in this “User Manual”. ASERVO EQUIHALER should only be administered in the left nostril of the horse. Following careful and proper insertion, the ASERVO EQUIHALER should have a snug fit in the left nostril. A snug fit is required to ensure the horse receives a complete dose of ASERVO EQUIHALER.

Contraindications:

Do not use in horses with known hypersensitivity to ciclesonide or corticosteroids.

Warnings / Precautions:

Human Warnings: Not for use in humans. Keep this and all medications out of the reach of children. In case of accidental inhalation, seek medical advice immediately and show the package insert or the product label to the physician.

People with known hypersensitivity to ciclesonide or any of the excipients should avoid contact with ASERVO EQUIHALER.

Animal Safety Warnings and Precautions: Safe use of ASERVO EQUIHALER has not been evaluated in pregnant or lactating mares.

Clinical and experimental data have demonstrated that corticosteroids administered orally or by injection to animals may induce the first stage of parturition if used during the last trimester of pregnancy and may precipitate premature parturition followed by dystocia, fetal death, retained placenta, and metritis. Additionally, corticosteroids administered during pregnancy can be teratogenic. Therefore, ASERVO EQUIHALER should only be used in pregnant mares if the potential benefit justifies the potential risk to the fetus.

Administration of corticosteroids may worsen existing bacterial, fungal, or viral infection. Secondary infections should be ruled out before prescribing ASERVO EQUIHALER. Inhaled corticosteroids should be used with caution, if at all, in horses with active infection of the respiratory tract. If clinical signs do not improve or worsen despite administration of ASERVO EQUIHALER, the prescriber should consider additional diagnostic evaluation.

Due to the potential for exacerbation of clinical signs of laminitis, glucocorticoids should be used with caution in horses with a history of laminitis, or horses otherwise at a higher risk for laminitis.

Use with caution in horses with chronic nephritis, equine pituitary pars intermedia dysfunction (PPID), and congestive heart failure.

Concurrent use of other anti-inflammatory drugs, such as non-steroidal anti-inflammatory drugs (NSAIDs) or other corticosteroids, should be approached with caution. Due to the potential for systemic exposure, concomitant use of NSAIDs and corticosteroids may increase the risk of gastrointestinal, renal, and other toxicity. Consider appropriate wash out times prior to administering NSAIDs or additional corticosteroids.

Other Warnings: Do not use in horses intended for human consumption.

Adverse Reactions:

The clinical safety of ASERVO EQUIHALER was assessed in a vehicle-controlled, randomized, double-blind 10-day field study followed by a 90-day open-label, extended-use field safety phase. In this field study, 319 client- or university-owned horses received either ASERVO EQUIHALER or vehicle control (the identical device containing the vehicle with no ciclesonide) during Phase 1.

Following Phase 1, 108 horses were enrolled in Phase 2, during which they could receive treatment for up to an additional 3 months. All horses in Phase 2 received the ASERVO EQUIHALER. Three hundred nineteen horses (163 ciclesonide and 156 control) of various breeds, 6 to 34 years of age, and weighing approximately 450 to 1,850 pounds were included in the field-study safety analysis. Adverse reactions that were reported in Phase 1 are listed in Table 1, and adverse reactions that were reported in Phase 2 are listed in Table 2.

The most common adverse reaction reported was coughing either during or immediately following inhalation of the test article (both ASERVO EQUIHALER and vehicle control groups).

Leukocytosis and/or neutrophilia developed in Phase 1 in several horses in both treatment groups, and in eight horses in Phase 2. Some of these horses also had concurrent clinical signs of infection, such as fever, which may have contributed to the leukocytosis. One ASERVO EQUIHALER-treated horse developed fever and leukocytosis characterized by a mature neutrophilia on Day 10 that was not present at screening. Other horses had possible alternate explanations for a stress leukogram, such as pain from a hoof abscess or poor acceptance of the device which may have caused stress from the study procedures.

In Phase 1, three ASERVO EQUIHALER-treated horses had increases in serum sorbitol dehydrogenase (SDH) above the reference range on Day 10 (high values were 12.4, 18.1 and 30.4 U/L); their baseline values were within the reference range (2-6 U/L). None of these horses had clinical signs attributable to elevated SDH levels. One horse also had an increase in serum gamma-glutamyltransferase (GGT) compared to baseline, but the GGT value at baseline was already above the reference range. By Day 40 of Phase 2, and again when measured at Day 100, this horse’s SDH and GGT values were within normal limits. In Phase 2, one horse developed an elevation in SDH (63.8 U/L) following the 6th course of ASERVO EQUIHALER treatment. This horse had elevations in alkaline phosphatase (269 U/L, reference range 76-262 U/L), aspartate aminotransferase (511 U/L, reference range 194-431 U/L), and GGT (128 U/L, reference range 9-37 U/L). Reported adverse events in this horse at various time points during the study included coughing, nasal discharge, tachycardia, and hyperthermia. After the visit at which abnormal blood work was detected, the owner opted to withdraw the horse from the study (approximately Day 75).

In Phase 1, one horse developed severe hives 30 minutes after the fourth dose of ASERVO EQUIHALER. This horse was removed from the study due to this adverse reaction.

Table 1: Number (%) of Horses with Adverse Reactions in Phase 1 of field study

Adverse Reaction | ASERVO EQUIHALER; (N=163); n (%) | Vehicle Control; (N=156); n (%)
Cough | 27 (16.6) | 27 (17.3)
Nasal Discharge | 17 (10.4) | 17 (10.9)
Leukocytosis and/or neutrophilia | 10 (6.1) | 7 (4.5)
Sneezing | 5 (3.1) | 3 (1.9)
Nasal irritation/bleeding | 2 (1.2) | 3 (1.9)
Increase in serum Sorbitol Dehydrogenase (SDH) | 3 (1.8) | 0 (0)
Hives | 1 (0.6) | 0 (0)

* Horses may have had one or more reports of a given adverse reaction

Table 2: Number (%) of Horses with Adverse Reactions in Phase 2 of field study

Adverse Reaction | ASERVO EQUIHALER; (N=100); n (%)
Cough | 12 (12%)
Nasal Discharge | 13 (13%)
Leukocytosis and/or neutrophilia | 8 (8%)
Nasal irritation/bleeding | 6 (6%)
Laminitis | 3 (3%)
Sneezing | 2 (2%)
Increase in serum Sorbitol Dehydrogenase (SDH) | 1 (1%)

* Horses may have had one or more reports of a given adverse reaction

Laminitis was reported in three horses during Phase 2. Two of the horses were noted to have a history of or physical evidence of prior laminitic episodes. The third horse had no prior history of laminitis, was initially treated for thrush, and responded to conservative therapy within a few weeks. No definitive diagnosis of laminitis was made, and the examining veterinarian concluded the horse’s environment played a role in the development of clinical signs.

In Phase 1, in both treatment groups, nasal soreness, bleeding, scabs in the nostril, and redness of the nostril were reported in five horses.

In Phase 2, horses were reported to have epistaxis (2 horses), blood tinged discharge (1 horse), nose bloody and raw (1 horse), sensitive nostril (1 horse), and bright pink color of nasal mucus membranes (1 horse). One case of epistaxis was reported 9 days after the last dose administered, and one case was reported from the right nostril less than 24 hours following the last dose. The blood tinged discharge from the left nostril was reported 11 days following the last dose administered. In Tables 1 and 2, these similar clinical signs are summarized as nasal irritation/bleeding.

To report suspected adverse drug events and/or obtain a copy of the Safety Data Sheet (SDS) or for technical assistance, contact Boehringer Ingelheim Animal Health USA Inc. at 888-637-4251. For additional information about adverse drug experience reporting for animal drugs, contact FDA at 1-888-FDA-VETS or online at www.fda.gov/reportanimalae

Information for Horse Owners:

Please review the User Manual with horse owners to ensure they understand the entire contents. The User Manual includes important instructions regarding the proper handling and use of ASERVO EQUIHALER. Demonstration of the activation, administration and storage of ASERVO EQUIHALER with the horse owner is highly recommended.

Clinical Pharmacology:

Pharmacokinetics: A four period pharmacokinetic study was conducted using 6 average weight horses and 6 light weight horses. Each horse received the following dosing regimens:

Period 1: 12 actuations (4116 mcg ciclesonide/horse) as a single inhalation administration,

Period 2: 16 actuations (5488 mcg ciclesonide/horse) as a single inhalation administration,

Period 3: 8 actuations (2744 mcg ciclesonide/horse) twice a day for 4 consecutive days and once on the fifth day,

Period 4: 8 actuations (2744 mcg ciclesonide/horse) twice a day for 5 consecutive days followed by 12 actuations (4116 mcg/horse) once a day for 5 days.

Blood samples were collected at pre-dose, 0 minutes, 5 minutes, 15 minutes, 30 minutes, and 1, 2, 4, 6, 8, 10, 12, and 24 hours after a single inhalation administration of 2744, 4116, and 5488 mcg in periods 1, 2, 3, and after multiple doses of 2744 and 4116 mcg in Periods 3 and 4.

Urine samples were collected at 24 and 48 hours in Period 4. Plasma and urine samples were analyzed for ciclesonide and des-ciclesonide concentrations using validated liquid chromatograph/ mass spectrometry methods.

Ciclesonide was rapidly metabolized to des-ciclesonide; there were quantifiable concentrations of des-ciclesonide in most horses at 5 minutes post-dose. Urine concentrations of ciclesonide and des-ciclesonide were below the limit of quantification at 24 and 48 hours after inhalation administration of 2744 mcg twice a day for 5 days followed by 4116 mcg once a day for 5 days. Table 3 summarizes the results of the pharmacokinetic analysis for des-ciclesonide in average and light weight horses (adjusted for body weight) after inhalations of 2744 mcg ciclesonide twice a day for 5 days followed by inhalations of 4116 mcg ciclesonide once a day for 5 days.

Table 3: Mean (± standard deviation; SD) pharmacokinetic parameters of des-ciclesonide after inhalations of 2744 mcg ciclesonide twice a day for 5 days followed by inhalations of 4116 mcg ciclesonide once a day for 5 days

Parameter | Dose (mcg) | Average Horse | Light Horse
Cmax (pg/mL) | 2744 | 232.67 (40.89) | 297.00 (92.0)
Tmax (hrs)† | 2744 | 0.50 (0.5-0.5) | 0.50 (0.25-1.0)
AUClast (hr*pg/mL) | 2744 | 824.26 (81.77) | 1087.07 (137.85)
t ½ (hrs) | 2744 | 5.00 (1.06) | 5.94 (2.12)
Cmax (pg/mL) | 4116 | 297.50 (104.62) | 493.00 (248.27)
Tmax (hrs)† | 4116 | 0.50 (0.5-1.0) | 0.50 (0.5-1.0)
AUClast (hr*pg/mL) | 4116 | 1011.39 (291.72) | 1550.31 (690.02)
t ½ (hrs) | 4116 | 6.08 (2.42) | 9.75 (4.20)

Cmax = maximum plasma concentration
†Tmax = time to maximum concentration; median (range)
AUClast = area under the concentration vs time curve to the last quantifiable concentration
t ½ = half-life

The drug exposure of des-ciclesonide was higher and more variable in the light weight horses compared to the average weight horses. For des-ciclesonide in both average and light weight horses, there was a greater than dose proportional increase in Cmax and AUClast with an increase in dose from 2744 to 4166 mcg, after a single dose. There was minimal accumulation of des-ciclesonide after inhalations of 2744 mcg ciclesonide twice a day for 5 days followed by inhalations of 4116 mcg ciclesonide once a day for 5 days.

Mode of Action: The affinity of des-ciclesonide to human and rat lung glucocorticoid receptors is 120 times greater than the parent compound’s affinity and 12 times greater than dexamethasone’s affinity. Des-ciclesonide’s anti-inflammatory properties are exerted via a wide range of inhibitory activities against cell types including mast cells, eosinophils, basophils, lymphocytes, macrophages, and neutrophils as well as against pro-inflammatory mediators such as histamine, eicosanoids, leukotrienes, and cytokines.

Effectiveness:

In a multi-center, vehicle-controlled, randomized, double-blind, field study, 320 horses were randomly allocated to receive either ASERVO EQUIHALER, the investigational veterinary product containing the active ingredient ciclesonide, or the control product, consisting of an identical inhaler device containing the vehicle with no ciclesonide. The study consisted of two phases, and 108 of the 320 enrolled horses participated in both Phase 1 and Phase 2 of the study.

Phase 1 of the study consisted of a double-blind, 10-day evaluation of the effectiveness and safety of ASERVO EQUIHALER compared to vehicle control for the management of clinical signs associated with severe equine asthma in both client- and university-owned horses under field conditions. Modifications of the horse’s environment were not allowed during Phase 1. Following completion of Phase 1, 108 horses participated in the 90-day open-label Phase 2 to evaluate the safety of ASERVO EQUIHALER during repeated use.

In Phase 1, a weighted clinical score (WCS) was calculated to assess both eligibility at study enrollment and treatment success at the conclusion of the study.

The WCS was comprised of nine clinical parameters (respiratory rate, nasal discharge, nasal flaring, abdominal lift, tracheal sounds, bronchial tones, crackles, wheeze, and cough) with a maximum score of 23. In order to enroll, horses were to have a WCS ≥11 (see Table 4), weigh at least 200 kg, have a diagnosis of severe equine asthma with observation of at least one clinical sign for 14 days or more prior to enrollment, have history of at least two previous episodes of labored breathing at rest, and have history of improvement with appropriate treatment (for example, glucocorticoid administration, bronchodilator administration, and/or change in environment). Two hundred fifty-eight horses (134 ASERVO EQUIHALER and 124 control) were included in the effectiveness analysis. Horses that were not fully dosed after enrollment due to the horse’s refusal to accept the device were included in the analysis as treatment failures.

Table 4: Weighted Clinical Score

Parameter | Score: Description
Respiratory rate (breaths/minute) | 0: <16 bpm; 1: 16-20 bpm; 2: 21-25 bpm; 3: 26-30 bpm; 4: >30 bpm
Nasal Discharge | 0: None; 1: Serous; 2: Mucous; 3: Mucopurulent
Nasal Flaring | 0: None; 1: Present
Abdominal Lift | 0: None; 1: Mild movement of abdomen and/or thorax and/or anus (with or without perceptible heaves line); 3: Pronounced movement of abdomen and/or thorax and/or anus (with or without perceptible heaves line)
Tracheal Sounds | 0: Normal; 1: Increase in intensity; 3: Mucus Movement
Bronchial Tones | 0: Normal; 2: Audible ventral and/or dorsal sounds
Crackles | 0: None; 2: Present
Wheezes | 0: None; 2: Present
Cough | 0: None; 1: Inducible by moderate pressure signal on larynx (only to be checked in the absence of intermittent or paroxysmal cough); 2: Intermittent; 3: Paroxysmal

A horse was considered a treatment success if there was a reduction in the WCS by at least 30% between Day 0/1 and Day 10, and had a Day 10 WCS ≤ 14. In this study, 52% of horses treated with ASERVO EQUIHALER vs. 33% of the horses treated with vehicle control had treatment success (p=0.0187), demonstrating the ASERVO EQUIHALER (ciclesonide inhalation spray) is effective for the management of clinical signs associated with severe equine asthma in horses.

Phase 2 provided field safety and use information for repeated 10-day courses of treatment under conditions of use, including use with other appropriate treatment strategies. During Phase 2, 88 horses completed the full 100-day study. The most common reason for early withdrawal was perceived lack of effectiveness (n=7). Horses were to be prescribed a 10-day course of the ASERVO EQUIHALER when the WCS was ≥9. Eight out of 108 did not receive additional inhaler devices. Of the 100 horses who qualified for retreatment, 52 (52%) qualified for one to three additional courses of treatment. Two horses that were in the ASERVO EQUIHALER group during Phase 1 received nine additional courses of treatment in Phase 2, resulting in 100 days of exposure to ASERVO EQUIHALER. Twenty-three (23%) horses received seven to nine courses of treatment during Phase 2. Concomitant medications and environmental changes intended for the overall management of severe equine asthma were allowed in Phase 2. The most commonly prescribed concomitant medications included bronchodilators and antihistamines. Systemic antimicrobials were prescribed in six horses where the clinical signs of severe equine asthma were not adequately controlled, clinical signs worsened despite continued administration of ASERVO EQUIHALER, or clinical signs of infection developed.

Two horses received dexamethasone at early study withdrawal because their disease was insufficiently controlled.

The most common environmental changes implemented during Phase 2 included soaking or steaming the hay, changing the forage source to either hay cubes or silage, changing the hay source (including stopping access to round bales), and increasing time out on pasture compared to time spent in the barn.

Animal Safety:

In a 1-month target animal safety study, 32 healthy adult horses (16 mares and 16 geldings) were assigned to 1 of 4 treatment groups, with 8 horses per group. Each treatment group contained 6 average weight horses (371.9 to 539.8 kg; mean 477.0 kg) and 2 light weight horses (121.5 to 260.5 kg; mean 179.5 kg). Light weight horses were specifically included to assess the safety of the highest mg ciclesonide/kg body weight dose.

Horses were randomized into four treatment groups, each receiving a different multiple of the therapeutic dose for 30 days (three times the treatment duration) administered with the nasal inhaler device. The treatment groups received 0X (vehicle control), 1X, 2X, and 3X the therapeutic dose of ciclesonide, respectively. Each treatment group included a total of 8 horses, six average weight horses (3 males and 3 females) and two light weight horses (1 male and 1 female). Horses in the control group received the same number of actuations as the highest dose group (3X) from the nasal inhaler device with vehicle only.

Mild mucoid to seromucoid nasal discharge was observed in all treatment groups, including controls, and did not appear to increase after treatment. In general, for the 0X, 2X, and 3X groups, the number of different fungal species isolated from the nares increased by Day 30; however, the result may have been an effect of extended time in the barn with direct contact with other horses and the environment rather than related to treatment with the inhaler. One horse cultured Candida species post-treatment, and that horse had no abnormal clinical signs. The dosing was intended to mimic twice daily dosing for the first 15 days, and then the once daily dosing for the second half of the study.

Facial asymmetry or deviation of the muzzle was observed in two horses during the study in the ciclesonide-treated groups. The signs resolved in one horse prior to the study conclusion.

No other related abnormal signs were observed, and no pathologic findings were correlated with this abnormality.

Cortisol levels were measured as a marker for suppression of the hypothalamic-pituitary-adrenal axis by systemic action of corticosteroids. Two light weight horses in the 3X ciclesonide-treatment group had values (16.3 and 14.1 ng/mL) that were lower than any other values recorded in the study (including baseline values and values from control horses), and lower than the normal reference range (27.6-73.2 ng/mL) on Day 14 (the end of the twice daily treatment period). At Day 29, one horse’s cortisol value returned to within the reference range (55.9 ng/mL) and the other remained low (15.9 ng/mL). These reductions in cortisol values in the smallest horses in the highest dose group may represent cortisol suppression from corticosteroid administration; however, neither of these horses had adverse events attributable to administration of ciclesonide.

Sorbitol dehydrogenase (SDH) levels were not statistically significantly different between ciclesonide treatment groups and the control group. However, one control horse (Day 14, SDH 13.6 U/L), one light weight horse in the 2X treatment group (Day 29, SDH 9.3 U/L), and two light weight horses in the 3X treatment group (Day 29, SDH values of 10.4 and 8.8 U/L) had SDH values that were above the reference range (reference range 1-8 U/L). These values did not correspond with increases in other liver enzymes and the horses remained clinically normal.

Storage Information:

Store at 15-30°C (59°-86°F), with excursions permitted up to 40°C (104°F). Protect from freezing.

Use within 12 days of activation.

How Supplied:

ASERVO EQUIHALER is supplied as one inhaler with a pre-inserted cartridge consisting of a plastic container crimped in an aluminum cylinder which contains inhalation solution for 140 treatment actuations (puffs).

Approved by FDA under NADA # 141-533

Marketed by:

Boehringer Ingelheim Animal Health USA Inc.

Duluth, GA 30096

Made in France

ASERVO® and EQUIHALER® are registered trademarks of Boehringer Ingelheim Vetmedica GmbH, used under license.

The Horse Head Logo is a trademark of Boehringer Ingelheim Animal Health USA Inc.

© 2020 Boehringer Ingelheim Animal Health USA Inc. All rights reserved.

449301-00

Revised 02/2020

Principal Display Panel – Label, 140 actuations (puffs)

NDC 0010-4493-01

Aservo® Equihaler®

(ciclesonide inhalation spray)

343 mcg/actuation

Glucocorticoid

For intranasal inhalation in horses only

140 actuations (puffs)

Principal Display Panel – Display Carton, 140 actuations (puffs)

NDC 0010-4493-01

Aservo® Equihaler

(ciclesonide inhalation spray)

343 mcg/actuation

Glucocorticoid

For intranasal inhalation in horses only

Caution: Federal law restricts this drug to use by or on the order of a licensed veterinarian.

Net Contents: 140 actuations (puffs)

Approved by FDA under NADA # 141-533